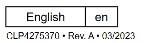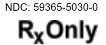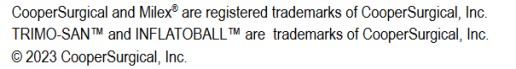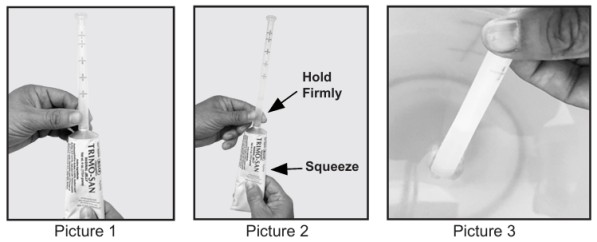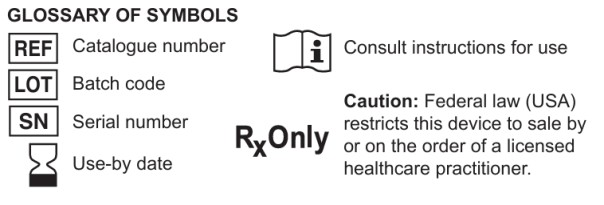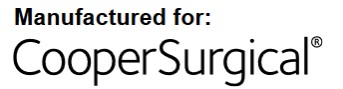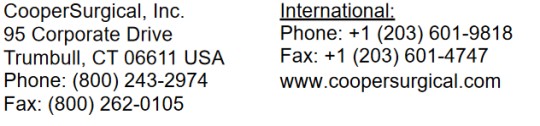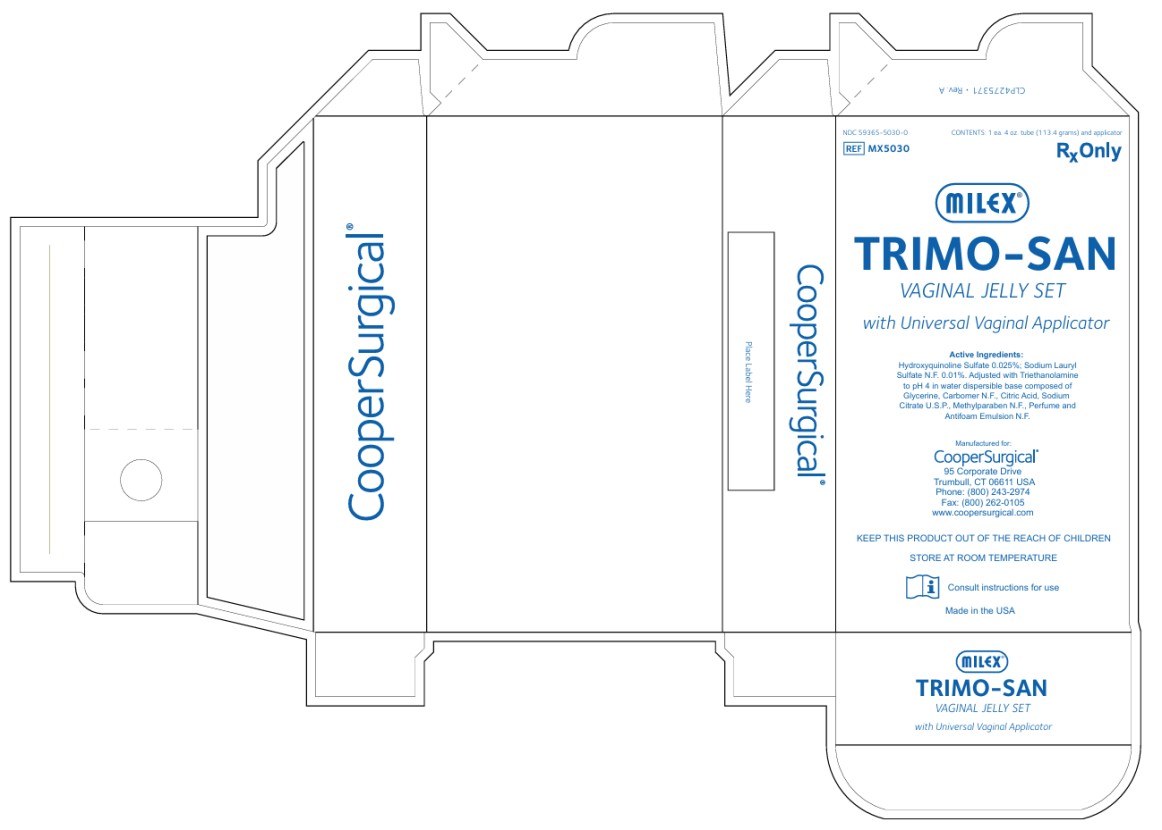 DRUG LABEL: TRIMO SAN
NDC: 59365-5030 | Form: JELLY
Manufacturer: CooperSurgical, Inc.
Category: prescription | Type: HUMAN PRESCRIPTION DRUG LABEL
Date: 20250903

ACTIVE INGREDIENTS: OXYQUINOLINE SULFATE 0.25 mg/1 g; SODIUM LAURYL SULFATE 0.1 mg/1 g
INACTIVE INGREDIENTS: CITRIC ACID MONOHYDRATE; SODIUM CITRATE; METHYLPARABEN; TROLAMINE

Trimo San

MX5030 ● Milex® TRIMO-SAN™ for Pessary Wearers

Instructions for Use

Please Read Carefully

A pessary is considered a foreign body in the vagina. For long-term pessary users, it is important to maintain the normal acidic pH of the vagina. TRIMO-SAN™, a deodorant vaginal gel, may help pessary wearers restore and maintain a normal acidic pH of the vagina.

CONTENTS:

Hydroxyquinoline Sulfate 0.025%; Sodium Lauryl Sulfate N.F. 0.01%. Adjusted with Triethanolamine to pH 4 in water dispersible base composed of Glycerine, Carbomer N.F., Citric Acid, Sodium Citrate U.S.P., Methylparaben N.F., Perfume and Antifoam Emulsion N.F.

STORAGE:

AFTER EACH USE Wipe threads of tube and the inside of the cap. RE-CAP TIGHTLY. Store at room temperature.

PURPOSE OF TRIMO-SAN

1. To help restore and maintain normal vaginal acidity.

2. To coat walls of vagina with a lubricating film that may help reduce odor-causing bacteria, since bacteria can flourish in abnormal vaginal pH.

INFORMATION ABOUT TRIMO-SAN

1. TRIMO-SAN Gel will not stain skin or natural fabrics.

2. TRIMO-SAN Gel helps eliminate odors, which may be associated with wearing a pessary.

3. Dosage of TRIMO-SAN Gel may be adjusted from one-half an applicator to a full applicator to obtain the desired results without messy leakage.

WARNING:

Chemicals in various preparations can interact with the pessary material resulting in discoloration or deterioration of the pessary.

TRIMO-SAN does not have a deleterious effect on any Milex pessary. Testing should be performed before using any other vaginal preparation with a pessary unless specifically prescribed by your healthcare professional.

TRIMO-SAN and PREGNANCY

TRIMO-SAN has NOT been tested for use during pregnancy.

- CooperSurgical does not recommend the use of TRIMO-SAN during pregnancy.
- If you wish to become pregnant, do not use TRIMO-SAN or any other personal hygiene product vaginally (douches, vaginal sprays, jellies or suppositories), for 6 hours prior to or following intercourse. Any product used within this time period could interfere with conception.

GENERAL INFORMATION

- New pessary wearers should use a ½ applicator (2g) of TRIMO-SAN 3 times the first week after original insertion of pessary.
- Use TRIMO-SAN ½ (2g) applicator twice a week thereafter unless otherwise directed by your healthcare professional.
- Reaction or irritation caused by TRIMO-SAN is very rare, but should it occur, discontinue use.
- If symptoms persist or worsen, contact your healthcare professional.

THIS PRODUCT IS INTENDED FOR MULTIPLE USE BY ONE PATIENT ONLY.

PROPER USE OF UNIVERSAL APPLICATOR

1. Unscrew cap from tube

2. Pierce end of tube with top of cap (a small amount of TRIMO-SAN may escape when top of tube is pierced).

3. Attach threaded end of the universal applicator to TRIMO-SAN tube (see picture 1). Applicator does not lock in place.

4. Firmly hold the applicator in place above the threads.

5. Squeeze the tube from the bottom while firmly holding the applicator against the tube until TRIMO-SAN reaches the specified dosage level (see picture 2).

6. Detach the Universal Applicator from the tube. Gently insert the Universal Applicator approximately ½ inch into the vagina.

Press in the plunger of the Universal Applicator to dispense the gel.

Keep the plunger pressed until the Universal Applicator is removed from the vagina.

NOTE: For those wearing an INFLATOBALL or CUBE pessary, remove the pessary per physician’s instruction before using TRIMO-SAN.

7. Clean the Universal Applicator immediately after use by flushing the Universal Applicator with water several times. Pull and press plunger back and forth while holding the opening of the applicator under water. (see picture 3). Make sure that the applicator is clean and dry before reusing.

8. After each use, wipe threads of tube and inside of cap. Recap tightly.

IMPORTANT IF YOU HAVE ANY OF THE FOLLOWING SIGNS OR SYMPTOMS, CONSULT A HEALTHCARE PROFESSIONAL

A. A discharge, which is unusual in color, consistency or amount.

B. A burning or itching sensation in the vaginal area.

C. A foul odor associated with vaginal discharge.

D. Any of the above especially if accompanied by unusual swelling or tenderness, fever, pains or cramps in the lower abdomen.

NOTE

If this product is being used with a pessary, follow your healthcare professional’s instructions explicitly. Consult your health care professional for all other medically-related advice.

PRINCIPAL DISPLAY PANEL

NDC 59365-5030-0
TRIMO-SAN
VAGINAL JELLY SET
with Universal Applicator
CONTENTS: 1 ea. 4 oz tube (113. 4 grams) and applicator
Rx Only

Revised: 4/2024